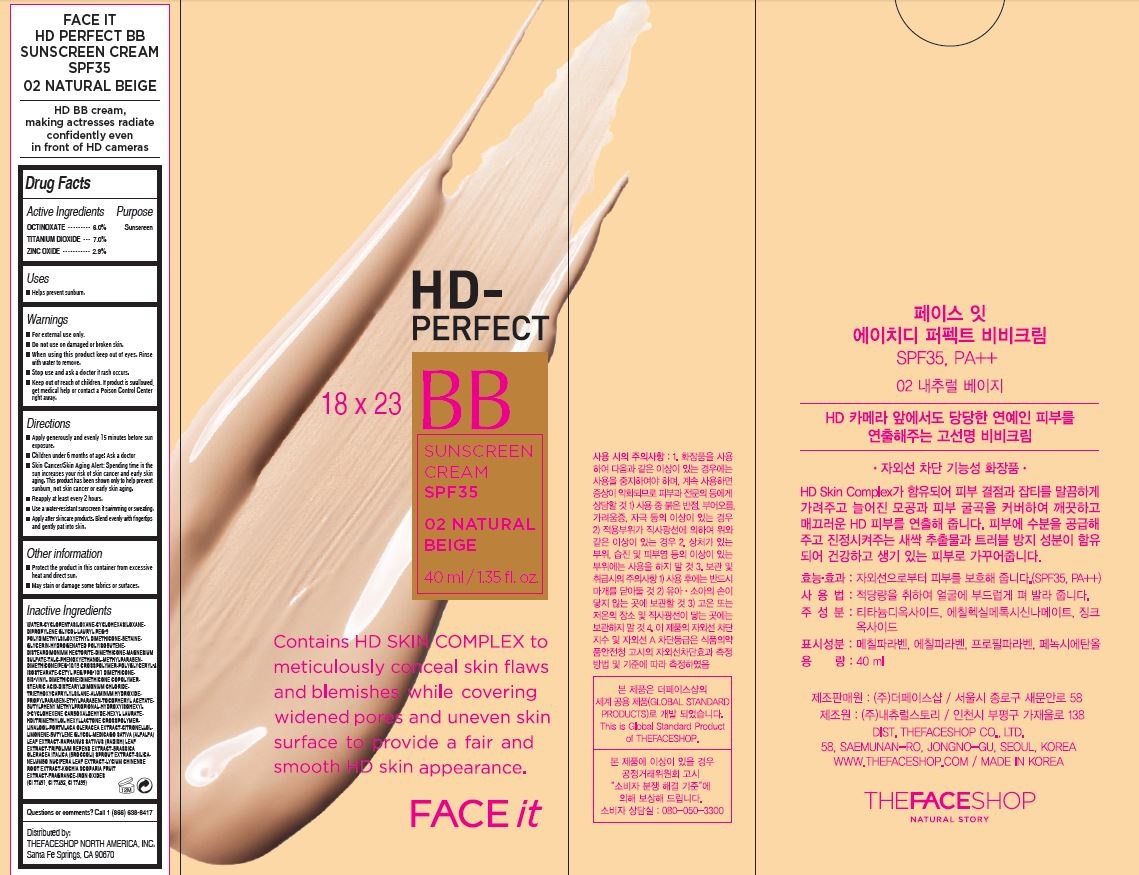 DRUG LABEL: FACE IT HD PERFECT BB
NDC: 51523-473 | Form: CREAM
Manufacturer: THEFACESHOP CO., LTD.
Category: otc | Type: HUMAN OTC DRUG LABEL
Date: 20141120

ACTIVE INGREDIENTS: TITANIUM DIOXIDE 2.8 g/40 mL; ZINC OXIDE 1.2 g/40 mL; OCTINOXATE 2.4 g/40 mL
INACTIVE INGREDIENTS: WATER

FACE IT HD PERFECT BB 32800473

Active Ingredients

OCTINOXATE ............6.0%

TITANIUM DIOXIDE... 7.0%

ZINC OXIDE................ 2.9%

Purpose

Sunscreen
Sunscreen
Sunscreen

Uses

Helps prevent sunburn.

Warnings

For external use only.

Do not use on damaged or broken skin.

Keep out of reach of children.

If product is swallowed, get medical help or contact a Poison Control Center

right away.

When using this product keep out of eyes.

Rinse with water to remove.

Stop use and ask a doctor if rash occurs.

Directions

Apply generously and evenly 15 minutes before sun

exposure.

Children under 6 months of age: Ask a doctor

Skin Cancer/Skin Aging Alert: Spending time in the

sun increases your risk of skin cancer and early skin

aging. This product has been shown only to help prevent

sunburn, not skin cancer or early skin aging.

Reapply at least every 2 hours.

Use a water-resistant sunscreen if swimming or sweating.

Apply after skincare products. Blend evenly with fingertips

and gently pat into skin.

Other information

Protect the product in this container from excessive

heat and direct sun.

May stain or damage some fabrics or surfaces.

Inactive Ingredients

WATER•CYCLOPENTASILOXANE•CYCLOHEXASILOXANE•

DIPROPYLENE GLYCOL•LAURYL PEG-9

POLYDIMETHYLSILOXYETHYL DIMETHICONE•BETAINE•

GLYCERIN•HYDROGENATED POLYISOBUTENE•

DISTEARDIMONIUM HECTORITE•DIMETHICONE•MAGNESIUM

SULFATE•TALC•PHENOXYETHANOL•METHYLPARABEN•

DIMETHICONE/PEG-10/15 CROSSPOLYMER•POLYGLYCERYL-4

ISOSTEARATE•CETYL PEG/PPG-10/1 DIMETHICONE•

BIS-VINYL DIMETHICONE/DIMETHICONE COPOLYMER•

STEARIC ACID•DISTEARYLDIMONIUM CHLORIDE•

TRIETHOXYCAPRYLYLSILANE•ALUMINUM HYDROXIDE•

PROPYLPARABEN•ETHYLPARABEN•TOCOPHERYL ACETATE•

BUTYLPHENY METHYLPROPIONAL•HYDROXYISOHEXYL

3-CYCLOHEXENE CARBOXALDEHYDE•HEXYL LAURATE•

HDI/TRIMETHYLOL HEXYLLACTONE CROSSPOLYMER•

LINALOOL•PORTULACA OLERACEA EXTRACT•CITRONELLOL•

LIMONENE•BUTYLENE GLYCOL•MEDICAGO SATIVA (ALFALFA)

LEAF EXTRACT•RAPHANUS SATIVUS (RADISH) LEAF

EXTRACT•TRIFOLIUM REPENS EXTRACT•BRASSICA

OLERACEA ITALICA (BROCCOLI) SPROUT EXTRACT•SILICA•

NELUMBO NUCIFERA LEAF EXTRACT•LYCIUM CHINENSE

ROOT EXTRACT•KOCHIA SCOPARIA FRUIT

EXTRACT•FRAGRANCE•IRON OXIDES

(CI 77491, CI 77492, CI 77499)

Questions or comments? Call 1 (866) 638-8417

Distributed by:

THEFACESHOP NORTH AMERICA, INC.

Santa Fe Springs, CA 90670

PACKAGE LABEL

HD PERFECT BB
SUNSCREEN CREAM SPF35
01 NATURAL BEIGE
Contains HD SKIN COMPLEX to meticulously conceal skin flaws
and blemishes while covering widened pores and uneven skin surface to provide a fair and smooth HD skin acceptance.
FACE it